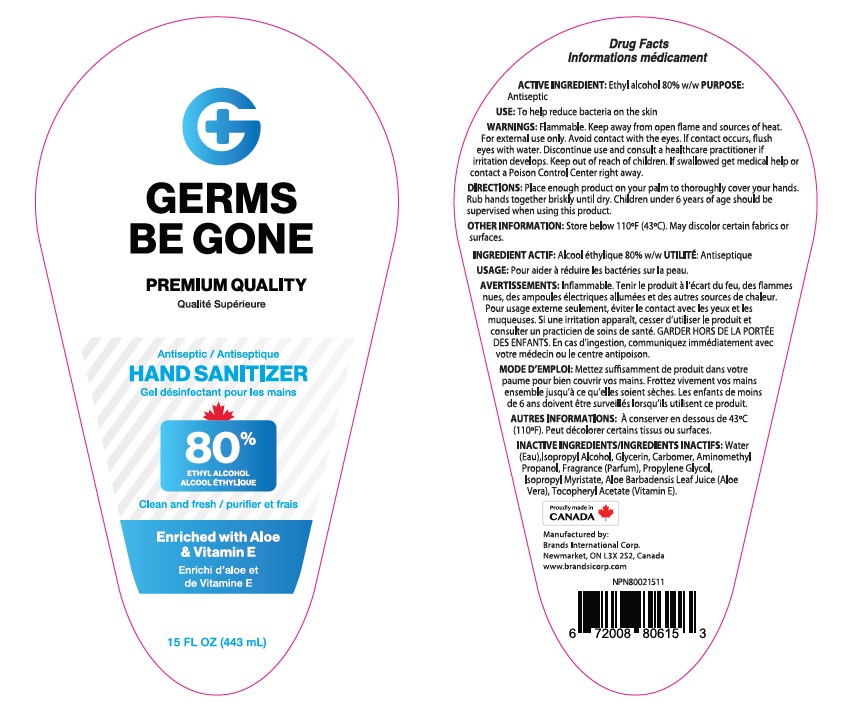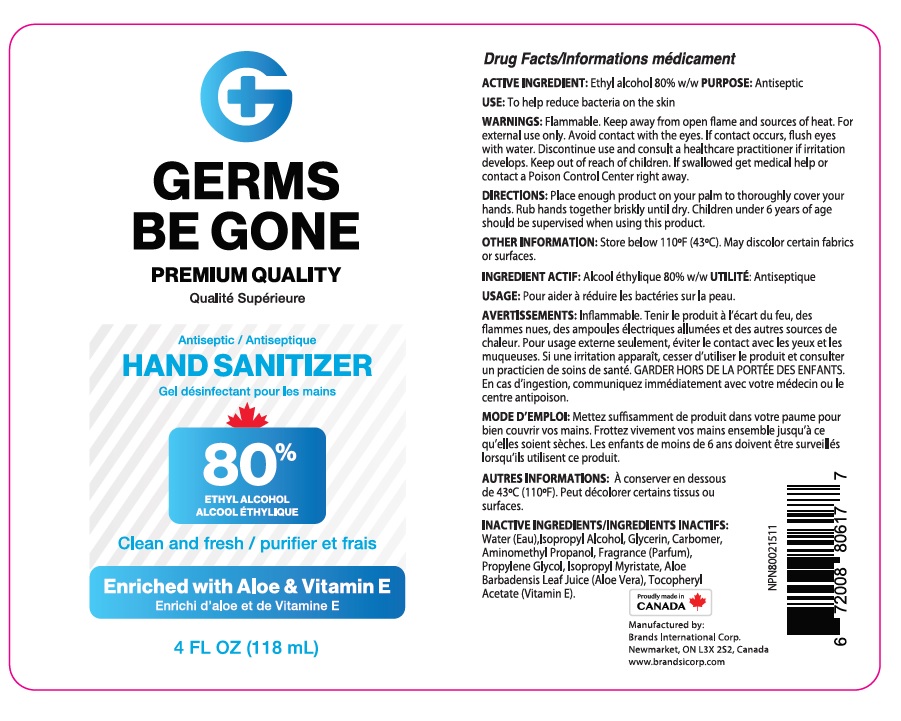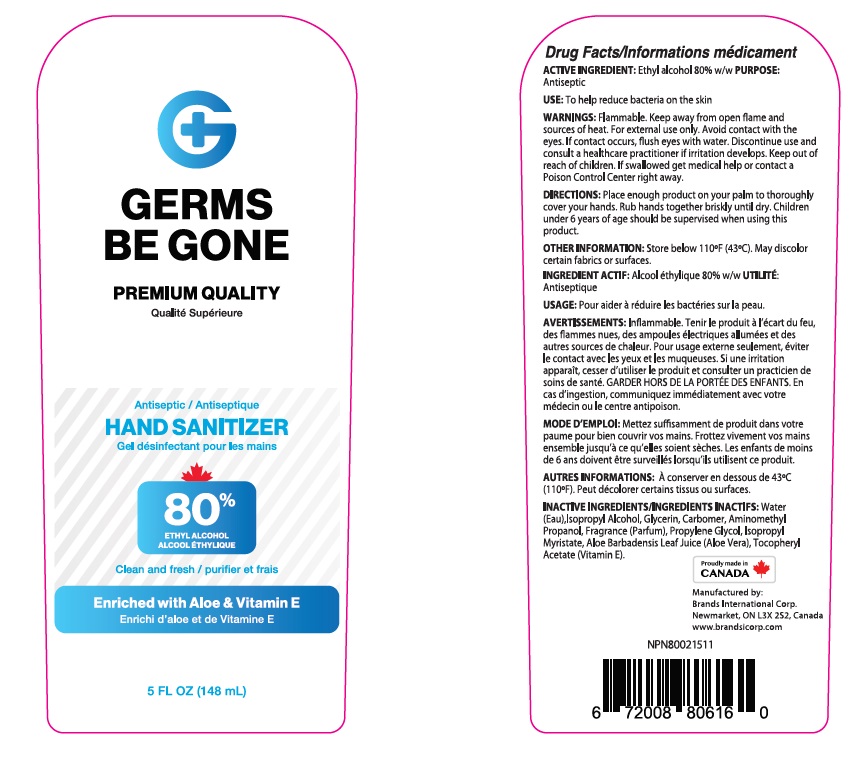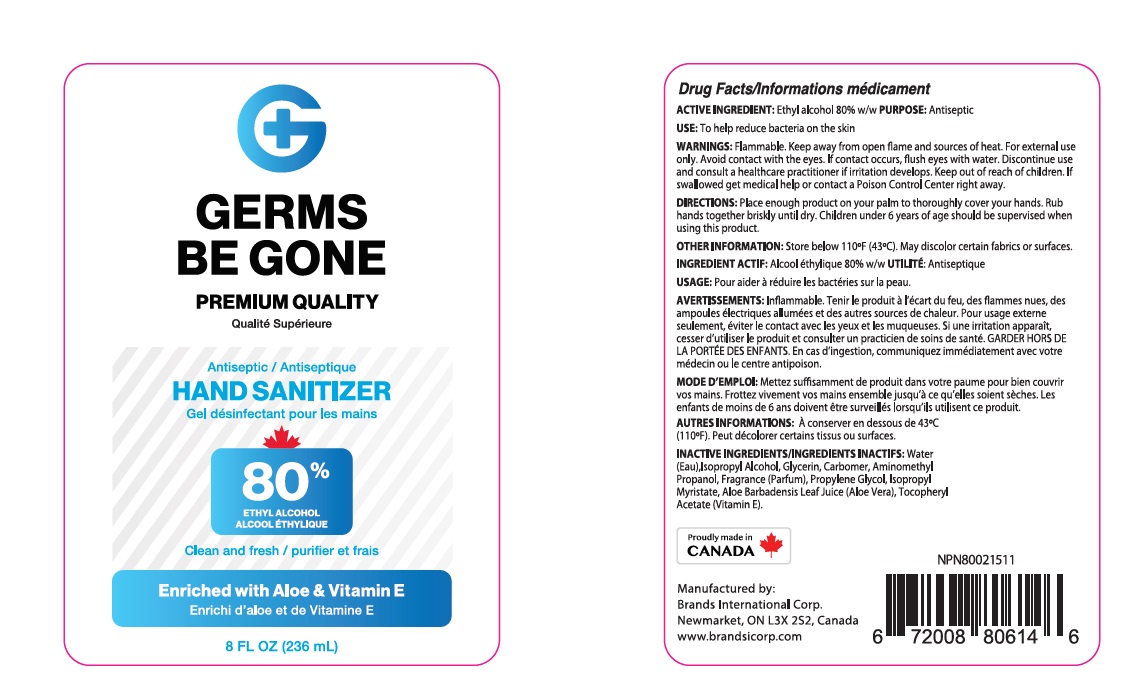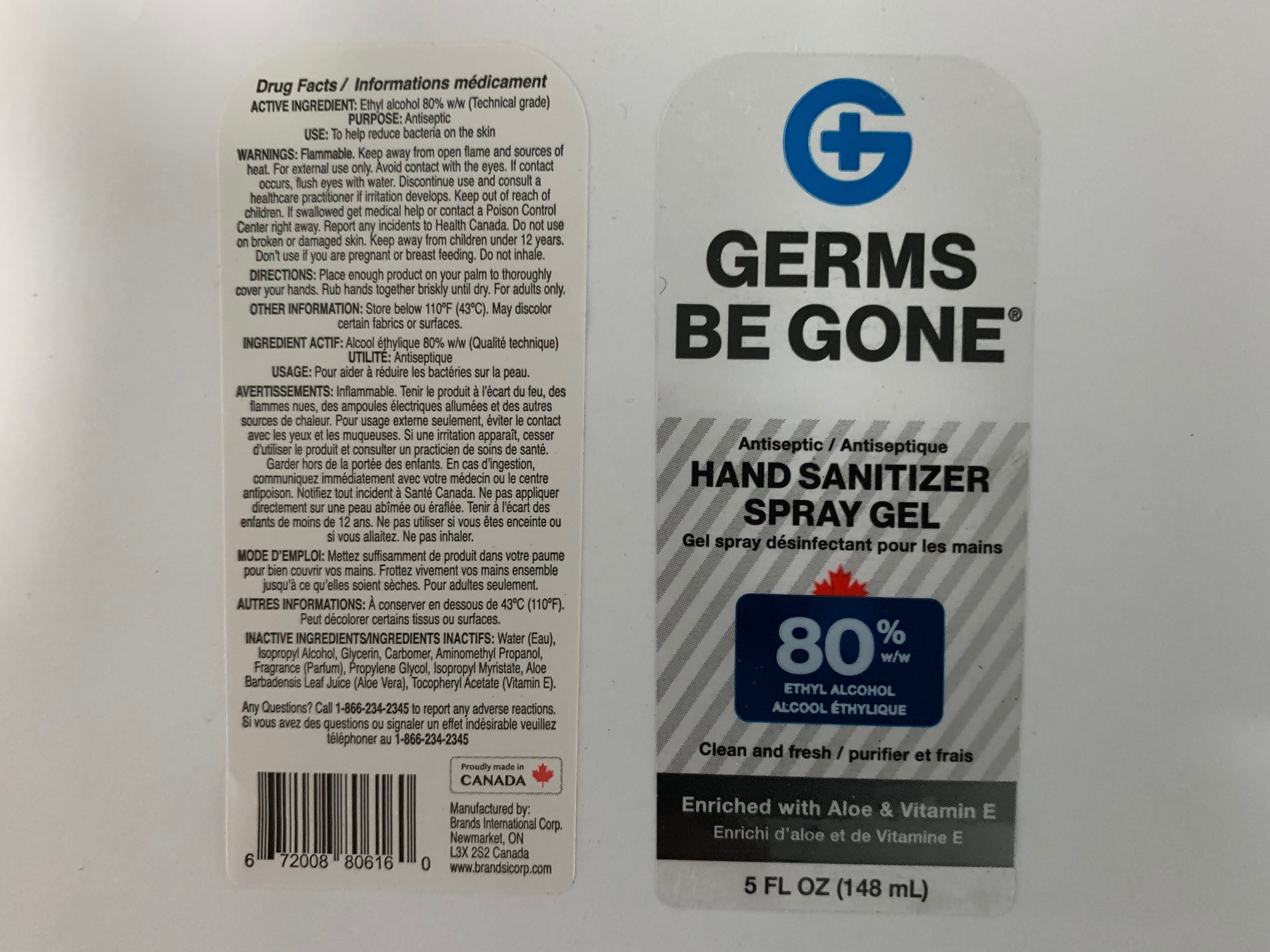 DRUG LABEL: Germs Be Gone Hand Sanitizer
NDC: 50157-503 | Form: GEL
Manufacturer: Brands International
Category: otc | Type: HUMAN OTC DRUG LABEL
Date: 20200516

ACTIVE INGREDIENTS: ALCOHOL 0.8 mL/1 mL
INACTIVE INGREDIENTS: WATER; ISOPROPYL ALCOHOL; ISOPROPYL MYRISTATE; ALOE VERA LEAF; PROPYLENE GLYCOL; GLYCERIN; CARBOMER COPOLYMER TYPE A; .ALPHA.-TOCOPHEROL ACETATE, D-; AMINOMETHYLPROPANOL

Germs be gone Hand Sanitizer

Active Ingredients

Ethyl Alcohol 80% w/w

Purpose: Antiseptic

Purpose

Antiseptic

Safety Instructions

Flammable, Keep away from fire and flame

Ask Doctor

Stop Use and Ask a doctor if irritation or redness develops

KEEP OUT OF REACH OF CHILDREN

If swallowed, get medical help or contact Poison Control right away

Other Information

Store below 110°F (43°C)
May discolor certain fabrics or surfaces.

Inactive Ingredients

water, isopropyl alcohol, glycerin, carbomer, aminomethyl propanol, fragrance, propylene glycol, Aloe, Tocopheryl Acetate. isopropyl myristate

Directions

- Place enough product in your palm to thoroughly cover your hands
- Rub hands together briskly until dry
- Children under 6 years of age should be supervised when using this product.

Warnings

For external use only.

Flammable. Keep away from fire or flame.

Uses

- helps reduce bacteria on the skin that could cause disease
- Recommended for repeated use

PACKAGE LABEL

NDC:

50157-503-01: 118ml

50157-503-02: 148ml

50157-503-05: 148ml : Bottle, Spray

50157-503-03: 236ml

50157-503-04: 443ml